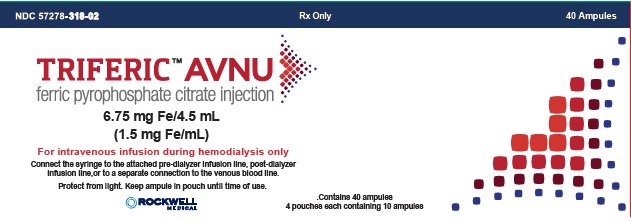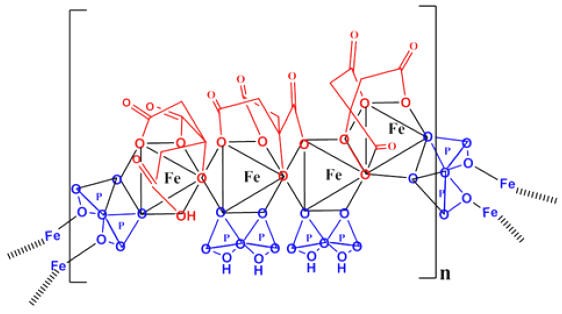 DRUG LABEL: Triferic AVNU
NDC: 57278-318 | Form: SOLUTION
Manufacturer: Rockwell Medical Inc.
Category: prescription | Type: HUMAN PRESCRIPTION DRUG LABEL
Date: 20200915

ACTIVE INGREDIENTS: FERRIC PYROPHOSPHATE CITRATE 1.5 mg/1 mL

HIGHLIGHTS OF PRESCRIBING INFORMATION

These highlights do not include all the information needed to use TRIFERIC AVNU safely and effectively. See full prescribing information for TRIFERIC AVNU.
TRIFERIC®AVNU (ferric pyrophosphate citrate injection), for intravenous use
Initial U.S. Approval: 2015

1. INDICATIONS AND USAGE

Triferic AVNU is an iron replacement product indicated for the replacement of iron to maintain hemoglobin in adult patients with hemodialysis-dependent chronic kidney disease (HDD-CKD). (1)

Limitations of Use

- Triferic AVNU is not intended for use in patients receiving peritoneal dialysis. (1)
- Triferic AVNU has not been studied in patients receiving home hemodialysis (1)

2. DOSAGE AND ADMINISTRATION

6.75 mg iron (III)_intravenously over 3 to 4 hours at each hemodialysis session via pre-dialyzer infusion line, post-dialyzer infusion line, or a separate connection to the venous blood line. (2.2)

3. DOSAGE FORMS AND STRENGTHS

Injection: 6.75 mg iron (III) per 4.5 mL solution (1.5 mg iron (III) per mL) in single-dose luer lock ampule (3)

4 CONTRAINDICATIONS

None

5. WARNINGS AND PRECAUTIONS

Hypersensitivity Reactions: Observe for signs and symptoms of hypersensitivity during and after hemodialysis and until clinically stable. (5.1)

6. ADVERSE REACTIONS

Most common adverse reactions (incidence ≥3%) are: headache, peripheral edema, asthenia, AV fistula thrombosis, urinary tract infection, AV fistula site hemorrhage, pyrexia, fatigue, procedural hypotension, muscle spasms, pain in extremity, back pain, and dyspnea. (6.1)

To report SUSPECTED ADVERSE REACTIONS, contact Rockwell Medical at 1-855-333-4315 or 1-248-960-9009 or FDA at 1-800-FDA-1088 or www.fda.gov/medwatch.

FULL PRESCRIBING INFORMATION

1. INDICATIONS AND USAGE

Triferic AVNU is an iron replacement product indicated for the replacement of iron to maintain hemoglobin in adult patients with hemodialysis-dependent chronic kidney disease (HDD-CKD).

Limitations of Use

- Triferic AVNU is not intended for use in patients receiving peritoneal dialysis.
- Triferic AVNU has not been studied in patients receiving home hemodialysis.

2. DOSAGE AND ADMINISTRATION

2.1 Recommended Dosage

The recommended dosage of Triferic AVNU is 6.75 mg iron (III) undiluted as a slow continuous intravenous infusion over 3 to 4 hours via the pre-dialyzer infusion line, post-dialyzer infusion line, or via a separate connection to the venous blood line during hemodialysis.

Administer Triferic AVNU at each dialysis procedure for as long as patients are receiving maintenance hemodialysis therapy for CKD.

The dosage of Triferic AVNU solution is expressed as mg of iron (III). Each mL of Triferic AVNU injection for intravenous administration contains 1.5 mg iron as iron (III).

2.2 Preparation and Administration

Each ampule of Triferic AVNU is intended for single-use only.

Use aseptic technique to prepare Triferic AVNU as follows:

- Visually inspect Triferic AVNU solution for signs of precipitation prior to use. The solution should be clear and slightly yellow-green in color.
- Holding the top of the ampule, shake with one single downward movement in order to remove the solution remaining in the cap.
- To open, twist the ampule body and the ampule head in opposite directions until the neck breaks off the top.
- Attach a 10 mL or 20 mL luer-lock syringe to the ampule and withdraw the contents (6.75 mg in 4.5 mL).
- Connect the syringe to the attached pre-dialyzer infusion line, post-dialyzer infusion line, or to a separate connection to the venous blood line.
- Mount the syringe on an infusion pump and administer as a slow continuous infusion of Triferic AVNU (4.5 mL) over 3 to 4 hours.
- Discard unused portion.

3. DOSAGE FORMS AND STRENGTHS

Injection: 6.75 mg iron (III) per 4.5 mL solution (1.5 mg iron (III) per mL) in single-dose luer lock ampule.

4 CONTRAINDICATIONS

None

5. WARNINGS AND PRECAUTIONS

Hypersensitivity Reactions: Observe for signs and symptoms of hypersensitivity during and after hemodialysis and until clinically stable.

5.1 Hypersensitivity Reactions

Serious hypersensitivity reactions, including anaphylactic-type reactions, some of which have been life-threatening and fatal, have been reported in patients receiving parenteral iron products. Patients may present with shock, clinically significant hypotension, loss of consciousness, and/or collapse. Monitor patients for signs and symptoms of hypersensitivity during and after hemodialysis until clinically stable. Personnel and therapies should be immediately available for the treatment of serious hypersensitivity reactions. [ see Adverse Reactions (6.1)]

Hypersensitivity reactions have been reported in 1 (0.3%) of 292 patients receiving ferric pyrophosphate citratein two randomized clinical trials.

5.2 Iron Laboratory Testing

Determine iron status on pre-dialysis blood samples. Post-dialysis serum iron parameters may overestimate serum iron and transferrin saturation.

6. ADVERSE REACTIONS

The following clinically significant adverse reactions are described below and elsewhere in the labeling:

- Hypersensitivity Reactions. [ see Warnings and Precautions (5.1)]

6.1 Clinical Trials Experience

Because clinical trials are conducted under widely varying conditions, adverse reaction rates observed in the clinical trials of a drug may not reflect the rates observed in practice.

The safety of ferric pyrophosphate citrate injection, for intravenous use, has been established based on adequate and well-controlled studies of ferric pyrophosphate citrate solution for hemodialysis [ see Clinical Studies (14)]. Below is a display of the adverse reactions of ferric pyrophosphate citrate solution for hemodialysis in these adequate and well-controlled studies.

The safety of ferric pyrophosphate citrate solution for hemodialysis was evaluated in 292 patients in two randomized, placebo-controlled clinical trials (CRUISE 1 (NCT01320202) and CRUISE 2 (NCT01322347)) who were administered ferric pyrophosphate citrate solution for hemodialysis usefor periods of up to 1 year[ see Clinical Studies (14)]. The mean total exposure in the randomized treatment period was 5 months. A total of 296 patients received placebo treatment for a similar time period. In the two studies, 64% were male and 54% were Caucasian. The median age of patients was 60 years (range, 20 to 89 years).

Adverse reactions occurring in 3% or greater of patients treated with ferric pyrophosphate citrate solution for hemodialysis use in the randomized clinical trials are listed in Table 1.

Table 1. Table 1: Adverse Reactions Reported in Two Clinical Trials in at Least 3% of Patients Receiving Ferric Pyrophoshate Citrate Solution for Hmodialysis Use and at an Incidence at Least 1% Greater than Placebo
Body System Adverse Reaction | Ferric Pyrophosphate Citrate; Solution for Hemodialysis Use N=292 n (%) | Placebo N=296 n (%)
Numberof patients with at least one adverse reaction | 229 (78) | 223 (75)
General Disorders and Administration Site Reactions
Peripheral edema | 20 (7) | 11 (4)
Pyrexia | 13 (5) | 9 (3)
Asthenia | 12 (4) | 9 (3)
Fatigue | 11 (4) | 6 (2)
Infections and Infestations
Urinary tract infection | 13 (5) | 4 (1)
Injury, Poisoning and Procedural Complications
Procedural hypotension | 63 (22) | 57 (19)
Arteriovenous fistula thrombosis | 10 (3) | 6 (2)
Arteriovenous fistula site hemorrhage | 10 (3) | 5 (2)
Musculoskeletal and Connective Tissue Disorders
Muscle spasms | 28 (10) | 24 (8)
Pain in extremity | 20 (7) | 17 (6)
Back pain | 13 (5) | 10 (3)
Nervous System Disorders
Headache | 27 (9) | 16 (5)
Respiratory, Thoracic and Mediastinal Disorders
Dyspnea | 17 (6) | 13 (4)

Other Adverse Reactions:

Less common adverse reactions occurring at a frequency of <3%:

- Hypersensitivity Reactions. [see Warnings and Precautions (5.1)]

Adverse Reactions Leading to Treatment Discontinuation:

In clinical trials,adverse reactionsleading to treatment discontinuation include headache, asthenia, dizziness, constipation,nausea,hypersensitivity reactions, intradialytic hypotension, pruritis and pyrexia.

8. USE IN SPECIFIC POPULATIONS

8.1 Pregnancy

Risk Summary

There are no available data on Triferic AVNU usein pregnant women to inform a drug-associated risk of major birth defects, miscarriage or adverse maternal or fetal outcomes. In animal reproduction studies, intravenous administration of ferric pyrophosphate citrate to pregnant rats and rabbits during organogenesis caused adverse developmental outcomes at maternally toxic dose levels that were higher than the maximum theoretical amount of iron transferred to patients from Triferic AVNU (see Data).

The estimated background risk of major birth defects and miscarriage for the indicated population is unknown. All pregnancies have a background risk of birth defect, loss, or other adverse outcomes. In the U.S. general population, the estimated background risk of major birth defects and miscarriage in clinically recognized pregnancies is 2-4% and 15-20%, respectively.

Data

Animal Data

In a fertility and early embryonic development study in female rats, the maternally toxic ferric pyrophosphate citrate dose of 40 mg/kg administered three times per week by intravenous infusion was not toxic to the developing embryo.

In embryo-fetal developmental toxicity studies, ferric pyrophosphate citrate was administered during the period of organogenesis as a one-hour intravenous infusion to pregnant rats and rabbits. No maternal or developmental toxicity was observed at doses up to 30 mg/kg/day in rats and 20 mg/kg/day in rabbits. Maternally toxic doses affected embryo-fetal development, resulting in post-implantation loss due to early resorptions, abnormal placentae, decreased fetal body weight and fetal head and vertebral malformations at 90 mg/kg/day in rats and vertebral malformations at 40 mg/kg/day in rabbits.

A pre-and post-natal development study was conducted in pregnant rats with intravenous doses of ferric pyrophosphate citrate up to 90 mg/kg/day. The maternally toxic dose of 90 mg/kg/day resulted in reductions in the number of live offspring and lower offspring body weights. There were no adverse effects on survival of offspring at doses up to 30 mg/kg/day, or on behavior, sexual maturation or reproductive parameters of offspring at any dose level.

8.2 Lactation

Risk Summary
There are no data on the presence of ferric pyrophosphate citrate in human milk, the effects on the breastfed child, or the effect on milk production. The developmental and health benefits of breastfeeding should be considered along with the mother’s clinical need for Triferic AVNU and any potential adverse effects on the breastfed child from Triferic AVNU or from the underlying maternal condition.

8.4 Pediatric Use

Safety and effectiveness have not been established in pediatric patients

8.5 Geriatric Use

In controlled clinical trials, 99 (29%) patients ≥ 65 years of age were treated with ferric pyrophosphate citrate. No overall differences in safety and efficacy were observed between older and younger patients in these trials [see Clinical Studies (14)].

11. DESCRIPTION

Triferic AVNU (ferric pyrophosphate citrate), an iron replacement product, is a mixed-ligand iron complex in which iron (III) is bound to pyrophosphate and citrate. It has a molecular formula of Fe4(C6H4O7)3(H2P2O7)2(P2O7)and a relative molecular weight of approximately 1313 daltons. Ferric pyrophosphate citrate has the following structure:

Triferic AVNU (ferric pyrophosphate citrate) injection is a clear, slightly yellow-green color sterile solution containing 6.75 mg of elemental iron (III) per 4.5 mL (1.5 mg iron (III) per mL) filled in a 5 mL low density polyethylene (LDPE) luer-lock ampule. Each Triferic AVNU ampule contains iron (0.14-0.17 % w/w), and less than 0.1% w/w citrate, pyrophosphate, phosphate, sodium and sulfate. One Triferic AVNU ampule is administered directly into the pre-dialyzer infusion line, post-dialyzer infusion line, or to a separate connection to the venous blood line over 3 to 4 hours.

12. CLINICAL PHARMACOLOGY

12.1 Mechanism of Action

Triferic AVNU contains iron in the form of ferric pyrophosphate citrate. Iron binds to transferrin for transport to erythroid precursor cells to be incorporated into hemoglobin.

12.2 Pharmacodynamics

Ferric pyrophosphate citrate exposure-response relationships and the time course of pharmacodynamics response are unknown.

Drug interaction Studies
In vitro studies showed that ferric pyrophosphate citrate did not impact the pharmacodynamics of unfractionated heparin or low molecular weight heparin.

12.3 Pharmacokinetics

Following administration of ferric pyrophosphate citrate 6.75 mg via a 3-hour intravenous infusion at a rate of 1.5 mg/hr (6.5 mg delivered), the total plasma iron and transferrin bound iron exposure values are provided in Table 2.

Table 2. Total Plasma Iron and Transferrin Bound Iron Exposure Parameters after Intravenous Administration of Ferric Pyrophosphate Citrate via the Pre-dialyzer and Post-dialyzer Infusion Line during Hemodialysis
Plasma Analyte | PK Parameter | Ferric Pyrophosphate Citrate
 |  | pre-dialyzer infusion line; (N-26) | post-dialyzer infusion line; (N=25)
Total Plasma Iron | Cmax (µg/dL) | 170 (24%) | 164 (23%)
 | AUC0-last (µg•h/dL) | 1260 (35%) | 1230 (33%)
*Transferrin Bound Iron | Cmax (µg/dL) | 180 (24%) | 169 (28%)
 | AUC0-last (µg•h/dL) | 1250 (37%) | 1190 (46%)
*N=17 for pre-dialyzer and N= 16 for post-dialyzer

13 NONCLINICAL PHARMACOLOGY

13.1 Carcinogenesis, Mutagenesis, Impairment of Fertility

Studies examining the carcinogenic potential of ferric pyrophosphate citrate have not been conducted.

Ferric pyrophosphate citrate was clastogenic in the in vitro chromosomal aberration assay in CHO cells in the presence of metabolic activation. Ferric pyrophosphate citrate was not mutagenic in the in vitro bacterial reverse mutation (Ames) test or clastogenic in the in vitro chromosomal aberration assay in CHO cells in the absence of metabolic activation or in the in vivo mouse micronucleus assay.

In a combined male and female fertility study in rats, ferric pyrophosphate citrate was administered intravenously over one hour three times per week at doses of up to 40 mg/kg. No adverse effects on fertility or reproduction were noted.

14. CLINICAL STUDIES

The efficacy of Triferic AVNU has been established based on adequate and well-controlled adult studies of ferric pyrophosphate citrate in iron replacement in patients with hemodialysis-dependent chronic kidney disease (HDD-CKD). Below is a display of the results of the adequate and well-controlled studies of ferric pyrophosphate citrate in this condition.

The efficacy of ferric pyrophosphate citrate in patients with HDD-CKD was assessed in two randomized, single blind, placebo-controlled clinical trials. Patients with hemoglobin of 9 g/dL to 12 g/dL with TSAT > 20% and serum ferritin concentrations > 200 mcg/L were enrolled. Patients were to remain in randomized treatment until pre-specified hemoglobin or ferritin criteria were met, indicating the need for a change in anemia management or if they completed 48 weeks. Ferric pyrophosphate citrate was added to bicarbonate concentrate with a final concentration of 110 mcg iron/L in the dialysate and was administered 3 or 4 times per week during hemodialysis. Most patients were receiving stable dose of erythropoiesis stimulating agents (ESAs) at baseline. After randomization, patients ESA doses were not to be changed.

In CRUISE 1 (NCT01320202), the mean age of patients was 58 years (range 23 to 89); 68% were male, 55% were Caucasian, 32% were African American, and 13% were other races.

In CRUISE 2 (NCT01322347), the mean age of patients was 58 years (range 20 to 89); 59% were male, 54% were Caucasian, 40% were African American, and 6% were other races.

Efficacy was assessed by the mean change in hemoglobin from baseline to the end-of-treatment period (average hemoglobin of the last one-sixth (1/6th) of the time in the randomized treatment period). About 18% of patientscompleted the planned 48 week treatment duration.

Table 3 shows the mean changes in hemoglobin (Hgb) and iron parameters in each treatment group from baseline to the end-of-treatment period for the ITT population.

Table 3 Changes from Baseline to end of Treatment in Hemoglobin, Ferritin, Reticulocyte Hgb (CHr) and Transferrin Saturation (TSAT)
 | CRUISE 1 |  | CRUISE 2
 | Ferric Pyrophsophate Citrate n=152 | Placebo n=153 | Ferric Pyrophosphate Citrate n=147 | Placebo n=147
Baseline Hemoglobin; Mean (SD), g/dL | 10.96 (0.592) | 10.91 (0.632) | 10.96 (0.605) | 10.94 (0.622)
Hemoglobin, Change from Baseline to End-of-Treatment MEan (SD), g/dL | -0.03 (1.147)* | -0.38 (1.24) | -0.08 (1.152)* | -0.44 (1.157)
Baseline Ferriitn; Mean (SD), mcg/L | 508.2 (193.55) | 509.3 (209.06) | 519.0 (201.56) | 478.4 (200.59)
Ferritin, Change from Baseline to End-of-Treatment; Mean (SD), mcg/L | -70.8 (132.41) | -141.2 (187.74) | -65.3 (162.45) | -120.9 (268.19)
Baseline Reticulocyte Hemoglobin (CHr); Mean (SD), pg | 32.37 (1.967) | 32.53 (1.965) | 32.56 (2.21) | 32.57 (1.932)
CHR, Change from Baseline to End-of-Treatment; Mean (SD), pg | -0.22 (1.191) | -0.90 (1.407) | -0.55 (1.441) | -0.85 (1.474)
Baseline TSAT; Mean (SD), % | 28.2 (8.23) | 27.1 (7.76) | 28.0 (8.15) | 28.2 (8.52)
TSAT, Change from Baseline to End-of-Treatment; MEan (SD), % | -1.0 (9.07) | -2.9 (7.65) | -0.9 (7.54) | -3.6 (7.29)
*p<0.05

16. HOW SUPPLIED / STORAGE AND HANDLING

16.1 How Supplied

Triferic AVNUinjection is a clear to slightly yellow-green solution available in single-dose luer lock ampules in the following package sizes:

NDC Code | Package Description | Amount/Total Volume (per ampule)
NDC 57278-318-01 | 10 Luer-lock ampules per pouch | 6.75 mg iron (III)/4.5 mL (1.5 mg iron (III) per mL)
NDC 57278-318-02 | 4 Pouches per Carton | 6.75 mg iron (III)/4.5 mL (1.5 mg iron (III) per mL)

16.2 Storage

Store ampules protected from light in the aluminum pouch at controlled room temperature (20° to 25°C [68° to 77°F]); excursions permitted to 15°-30°C (59° to 86°F) [See USP Controlled Room Temperature]. Do not freeze.

17. PATIENT COUNSELING INFORMATION

Prior to the administration of Triferic AVNU:

- Question patients regarding any prior history of reactions to parenteral iron products.
- Advise patients of the risk of hypersensitivity reactions associated with Triferic AVNU.
- Advise patient to report any signs and symptoms of hypersensitivity that may develop during and after the dialysis session, such as rash, itching, dizziness, lightheadedness, swelling and breathing problems [ see Warnings and Precautions (5)].

Manufactured for

Rockwell Medical, Inc.

30142 S Wixom Rd

Wixom, MI 48393

PRINCIPAL DISPLAY PANEL - TRIFERIC AVNU 40 Ampule Carton

NDC 57278-318-02

40 Amplules in 4 -10 Ampule pouches

Rx Only

Triferic AVNU®

ferric pyrophosphate citrate injection

6.75 mg Fe/4.5 ml (1.5 mg Fe/mL)

Protect from Light

For intravenous infusion during hemodialysis only
Connect the syringe to the attached pre-dialyzer infusion line, post-dialyzer infusion line,or to a separate connection to the venous blood line.
Protect from light. Keep ampule in pouch until time of use.